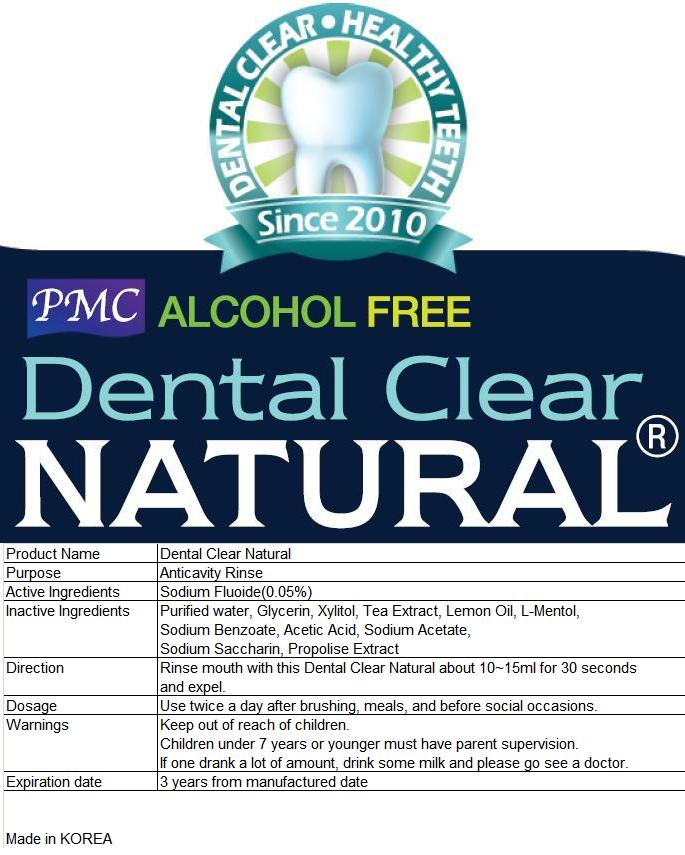 DRUG LABEL: Dental Clear Natural
NDC: 24765-100 | Form: RINSE
Manufacturer: Pharmacal-International. Co., Ltd.
Category: otc | Type: HUMAN OTC DRUG LABEL
Date: 20111201

ACTIVE INGREDIENTS: Sodium fluoride 0.05 mL/100 mL
INACTIVE INGREDIENTS: Water; LEVOMENTHOL; GLYCERIN; ACETIC ACID; SODIUM ACETATE; CAMELLIA SINENSIS ROOT; SACCHARIN SODIUM DIHYDRATE; SODIUM BENZOATE; XYLITOL; POLOXAMER 124; CITRUS LIMON FRUIT OIL; MALIC ACID; PROPOLIS WAX

Drug Facts

ACTIVE INGREDIENT

Sodium Fluoride (0.05%)

PURPOSE

Anticavity Rinse

Keep out of reach of children.

Children under 7 years or younger must have parent supervision.

If one drank a lot of amount, drink some milk and please go see a doctor.

Keep out of reach of children.

INDICATIONS AND USAGE

Use twice a day after brushing, meals, and before social occasions.

DOSAGE AND ADMINISTRATION

Rinse mouth with this Dental Clear Natural about 10 -15 ml for 30 seconds and expel.

INACTIVE INGREDIENT

Water

L-Menthol

Glycerin

Acetic Acid

Sodium Acetate

Camellia Sinensis leaf Extract

Saccharin sodium

Sodium benzoate

Xylitol

Poloxamer

Citrus Medica Limonum Peel Oil

Malic Acid

Propolis Exxtract